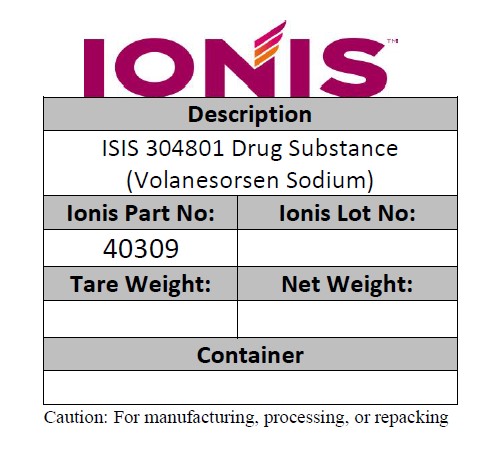 DRUG LABEL: NA
NDC: 72126-001 | Form: POWDER
Manufacturer: Akcea Therapeutics, Inc.
Category: other | Type: BULK INGREDIENT
Date: 20230524

ACTIVE INGREDIENTS: VOLANESORSEN SODIUM 1 kg/1 kg

PACKAGE LABEL

Description of ISIS 304801 Drug Substance (Volanesorsen Sodium)

Ionis Part No. 40309